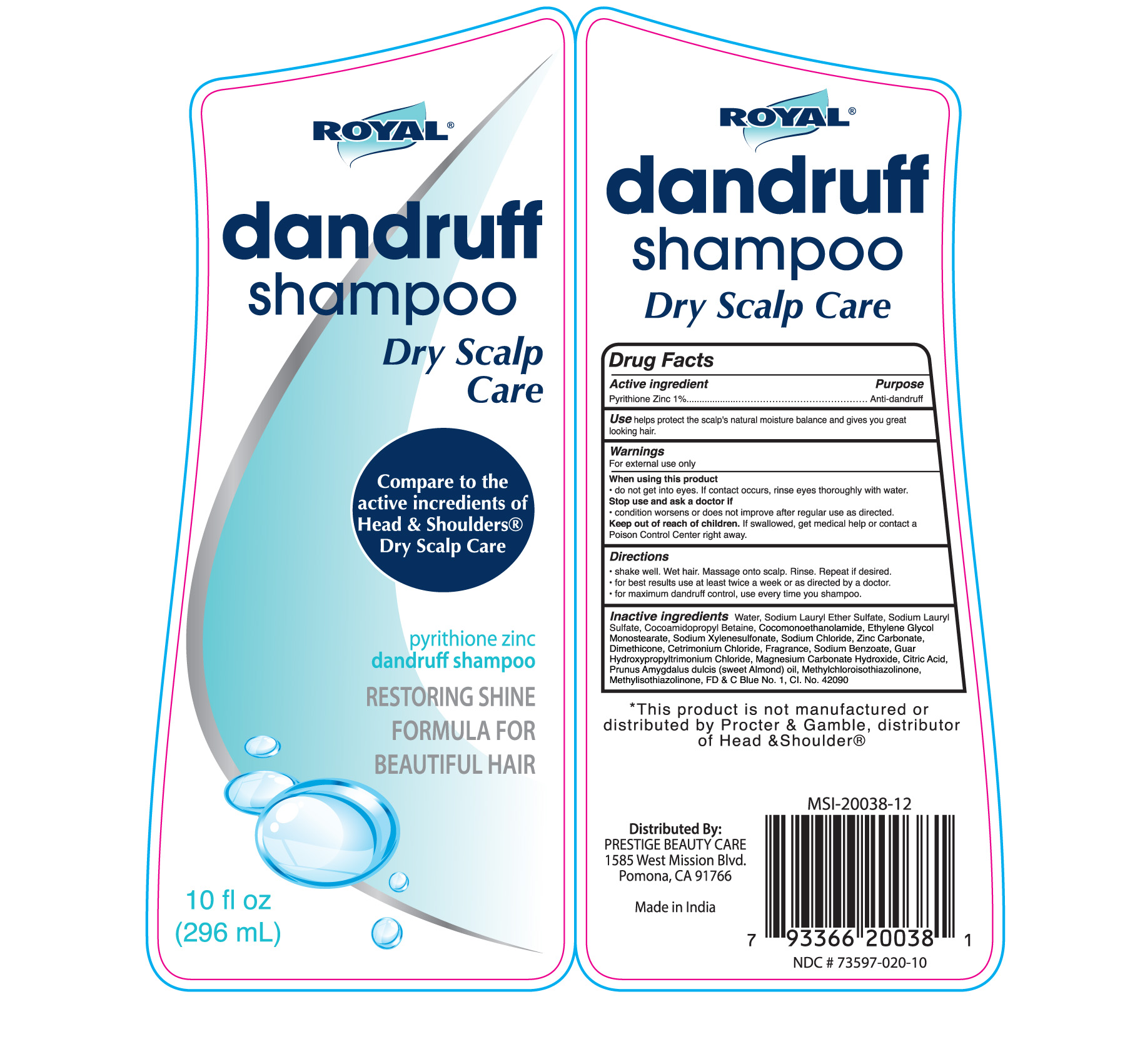 DRUG LABEL: Royal Dandruff Dry Scalp
NDC: 73597-020 | Form: SHAMPOO
Manufacturer: Mission Series Inc. dba Prestige Beauty Care
Category: otc | Type: HUMAN OTC DRUG LABEL
Date: 20250108

ACTIVE INGREDIENTS: PYRITHIONE ZINC 1 g/100 g
INACTIVE INGREDIENTS: GLYCOL STEARATE; COCAMIDOPROPYL BETAINE; WATER; METHYLISOTHIAZOLINONE; ZINC CARBONATE; MAGNESIUM CARBONATE HYDROXIDE; ALMOND OIL; FD&C BLUE NO. 1; SODIUM XYLENESULFONATE; SODIUM CHLORIDE; COCO MONOETHANOLAMIDE; CETRIMONIUM CHLORIDE; METHYLCHLOROISOTHIAZOLINONE; CITRIC ACID MONOHYDRATE; GUAR HYDROXYPROPYLTRIMONIUM CHLORIDE (1.7 SUBSTITUENTS PER SACCHARIDE); SODIUM LAURYL SULFATE; DIMETHICONE; SODIUM LAURETH SULFATE; SODIUM BENZOATE

Royal Dandruff Dry Scalp

Active Ingredient

Active Ingredient - Pyrithione Zinc 1%

Purpose

Anti-dandruff

Use

Use - helps protect the scalp's natural moisture balance and gives you great looking hair.

Warnings

Warnings - For external use only.

When using this product

- do not get into eyes. If contact occurs, rinse eyes thoroughly with water.

Stop Use

Stop use and ask a doctor if

- condition worsens or does not improve after regular use as directed.

Keep out of reach of children. If swallowed, get medical help or contact a Poison Control Center right away.

Directions

- shake well. Wet hair. Massage onto scalp. Rinse. Repeat if desired.

- for best results use at least twice a week or as directed by a doctor.

- for maximum dandruff control, use every time you shampoo.

Inactive Ingredients

Inactive Ingredients - Water, Sodium Lauryl Ether Sulfate, Sodium Lauryl Sulfate, Cocoamidopropyl Betaine, Cocomonoethanolamide, Ethylene Glycol Monostearate, Sodium Xylenesulfonate, Sodium Chloride, Zinc Carbonate, Dimethicone, Cetrimonium Chloride, Fragrance, Sodium Benzoate, Guar Hydroxypropyltrimonium Chloride, Magnesium Carbonate Hydroxide, Citric Acid, Prunus Amygdalus dulcis (sweet Almond) oil, Methylchloroisothiazolinone, Methylisothiazolinone, FD & C Blue No. 1, Cl. No. 42090

Distributed By

PRESTIGE BEAUTY CARE

1585 West Mission Blvd.

Pomona, CA 91766

Made in India